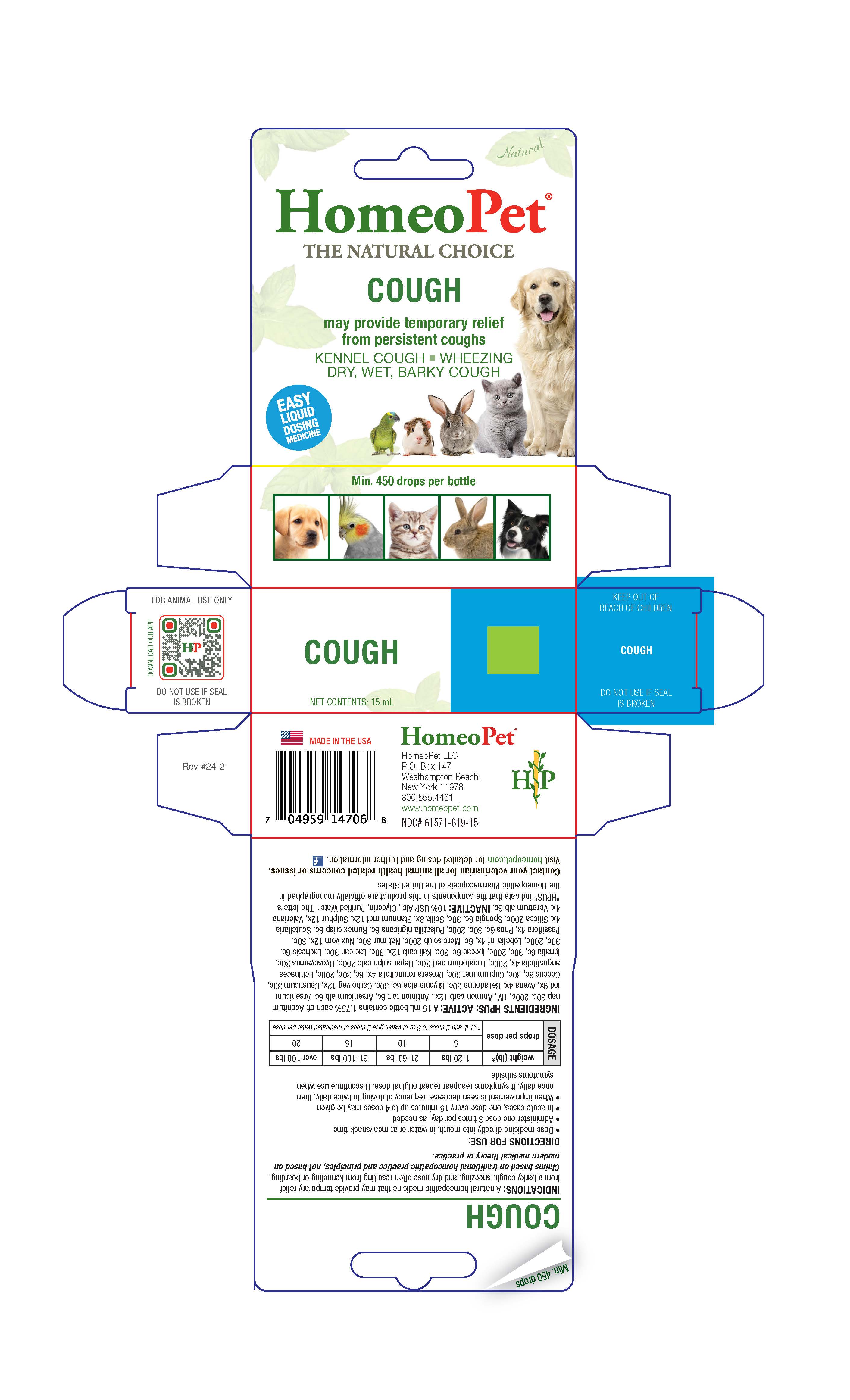 DRUG LABEL: COUGH
NDC: 61571-619 | Form: LIQUID
Manufacturer: HomeoPet, LLC
Category: homeopathic | Type: OTC ANIMAL DRUG LABEL
Date: 20251216

ACTIVE INGREDIENTS: ACONITUM NAPELLUS 30 [hp_C]/15 mL; AMMONIUM CARBONATE 12 [hp_X]/15 mL; Antimony potassium tartrate 6 [hp_C]/15 mL; ARSENIC TRIOXIDE 6 [hp_C]/15 mL; ARSENIC TRIIODIDE 9 [hp_X]/15 mL; AVENA SATIVA FLOWERING TOP 4 [hp_X]/15 mL; ATROPA BELLADONNA 30 [hp_C]/15 mL; BRYONIA ALBA ROOT 6 [hp_C]/15 mL; ACTIVATED CHARCOAL 12 [hp_X]/15 mL; CAUSTICUM 30 [hp_C]/15 mL; PROTORTONIA CACTI 6 [hp_C]/15 mL; COPPER 30 [hp_C]/15 mL; DROSERA ROTUNDIFOLIA 4 [hp_X]/15 mL; ECHINACEA ANGUSTIFOLIA 4 [hp_X]/15 mL; EUPATORIUM PERFOLIATUM FLOWERING TOP 30 [hp_X]/15 mL; CALCIUM SULFIDE 200 [hp_C]/15 mL; HYOSCYAMUS NIGER 30 [hp_C]/15 mL; STRYCHNOS IGNATII SEED 6 [hp_C]/15 mL; IPECAC 6 [hp_C]/15 mL; POTASSIUM CARBONATE 12 [hp_X]/15 mL; CANIS LUPUS FAMILIARIS MILK 30 [hp_C]/15 mL; LACHESIS MUTA VENOM 6 [hp_C]/15 mL; LOBELIA INFLATA 4 [hp_X]/15 mL; MERCURIUS SOLUBILIS 200 [hp_C]/15 mL; SODIUM CHLORIDE 30 [hp_C]/15 mL; STRYCHNOS NUX-VOMICA SEED 12 [hp_X]/15 mL; PASSIFLORA INCARNATA FLOWERING TOP 4 [hp_X]/15 mL; PHOSPHORUS 6 [hp_C]/15 mL; PULSATILLA PRATENSIS 6 [hp_C]/15 mL; RUMEX CRISPUS ROOT 6 [hp_C]/15 mL; SCUTELLARIA LATERIFLORA 4 [hp_C]/15 mL; SILICON DIOXIDE 200 [hp_C]/15 mL; SPONGIA OFFICINALIS SKELETON, ROASTED 6 [hp_C]/15 mL; DRIMIA MARITIMA BULB 8 [hp_X]/15 mL; TIN 12 [hp_X]/15 mL; SULFUR 12 [hp_X]/15 mL; VALERIAN 4 [hp_X]/15 mL; VERATRUM ALBUM ROOT 6 [hp_C]/15 mL
INACTIVE INGREDIENTS: ALCOHOL; WATER; GLYCERIN

COUGH

Cough

May provide temporary relief from persisten coughs

KENNEL COUGH - WHEEZING- DRY, WET, BARKY COUGH

Directions for Use and Dosage

- Dose remedy directly into mouth, in water or at meal/snack time
- Administer one dose 3 times per day, as needed
- In acute cases, one dose every 15 minutes up to 4 doses may be given
- When improvement is seen decrease frequency of dosing to twice daily, then once daily. If symptoms reappear repeat original dose. Discontinue use when symptoms subside.

weight (lb)* | drops per dose
1-20 | 5
21-60 | 10
61-100 | 15
over 100 | 20
*<1 lb add 2 drops to 8 oz of water, give 2 drops of medicated water per dose.

Contact veterinarian

Contact your veterinarian for all animal health related concerns or issues.

Visit homeopet.com for detailed dosing and further information.

Ingredients HPUS: ACTIVE:

Aconitum nap 30c, 200c, 1M, Ammon carb 12x , Antimon tart 6c, Arsenicum alb 6c, Arsenicum iod 9x, Avena 4x, Belladonna 30c, Bryonia alba 6c, 30c, Carbo veg 12x, Causticum 30c, Coccus 6c, 30c, Cuprum met 30c, Drosera rotundifolia 4x, 6c, 30c, 200c, Echinacea angustifolia 4x, 200c, Eupatorium perf 30c, Hepar Sulph calc 200c, Hyoscyamus 30c, Ignatia 6c, 30c, 200c, Ipecac 6c, 30c, Kali carb 12x, 30c, Lac can 30c, Lachesis 6c, 30c, 200c, Lobelia inf 4x, 6c, Merc solub 200c, Nat mur 30c, Nux vom 12x, 30c, Passiflora 4x, Phos 6c, 30c, 200c, Pulsatilla nigricans 6c, Rumex crisp 6c, Scutellaria 4x, Silicea 200c, Spongia 6c, 30c, Scilla maritima 8x, Stannum met 12x, Sulphur 12x, Valeriana 4x, Veratrum alb 6c.

Inactive Ingredients

USP Alcohol, Purified Water, Glycerin

Indications

A natural homeopathic medicine that may provide temporary relief from a barky cough, sneezing, and dry nose often resulting from kenneling or boarding. Claims based on traditional homeopathic practice and principles, not based on modern medical theory or practice.